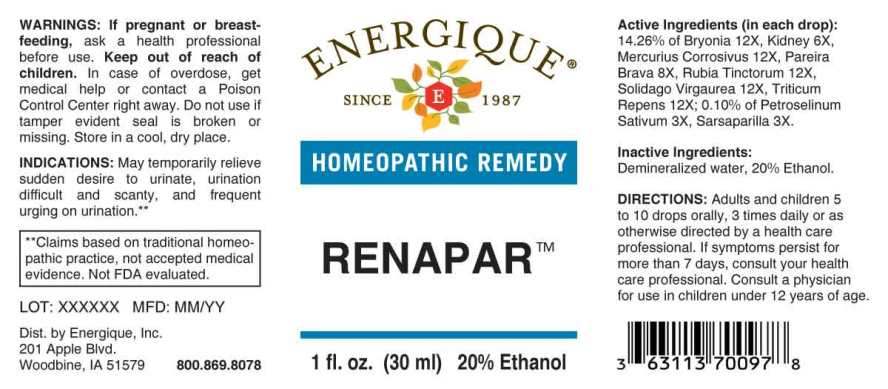 DRUG LABEL: Renapar
NDC: 44911-0641 | Form: LIQUID
Manufacturer: Energique, Inc.
Category: homeopathic | Type: HUMAN OTC DRUG LABEL
Date: 20231201

ACTIVE INGREDIENTS: CHONDRODENDRON TOMENTOSUM ROOT 8 [hp_X]/1 mL; PETROSELINUM CRISPUM WHOLE 3 [hp_X]/1 mL; SMILAX ORNATA ROOT 3 [hp_X]/1 mL; PORK KIDNEY 6 [hp_X]/1 mL; BRYONIA ALBA ROOT 12 [hp_X]/1 mL; MERCURIC CHLORIDE 12 [hp_X]/1 mL; RUBIA TINCTORUM ROOT 12 [hp_X]/1 mL; SOLIDAGO VIRGAUREA FLOWERING TOP 12 [hp_X]/1 mL; ELYMUS REPENS ROOT 12 [hp_X]/1 mL
INACTIVE INGREDIENTS: WATER; ALCOHOL

DRUG FACTS:

ACTIVE INGREDIENTS:

(in each drop): 14.26% of Bryonia (Alba) 12X, Kidney (Suis) 6X, Mercurius Corrosivus 12X, Pareira Brava 8X, Rubia Tinctorum 12X, Solidago Virgaurea 12X, Triticum Repens 12X; 0.10% of Petroselinum Sativum 3X, Sarsaparilla (Smilax Regelii) 3X.

INDICATIONS:

May temporarily relieve sudden desire to urinate, urination difficult and scanty, and frequent urging on urination.**

**Claims based on traditional homeopathic practice, not accepted medical evidence. Not FDA evaluated.

WARNINGS:

If pregnant or breastfeeding, ask a health professional before use.

Keep out of reach of children. In case of overdose, get medical help or contact a Poison Control Center right away.

Do not use if tamper evident seal is broken or missing.

Store in a cool, dry place.

KEEP OUT OF REACH OF CHILDREN:

In case of overdose, get medical help or contact a Poison Control Center right away.

DIRECTIONS:

Adults and children 5 to 10 drops orally, 3 times daily or as otherwise directed by a health care professional. If symptoms persist for more than 7 days, consult your health care professional. Consult a physician for use in children under 12 years of age.

INDICATIONS:

May temporarily relieve sudden desire to urinate, urination difficult and scanty, and frequent urging on urination.**

**Claims based on traditional homeopathic practice, not accepted medical evidence. Not FDA evaluated.

INACTIVE INGREDIENTS:

Demineralized water, 20% Ethanol.

QUESTIONS:

Dist. by Energique, Inc.

201 Apple Blvd

Woodbine, IA 51579 800.869.8078

PACKAGE LABEL DISPLAY:

ENERGIQUE

SINCE 1987

HOMEOPATHIC REMEDY

RENAPAR

1 fl. oz. (30 ml)